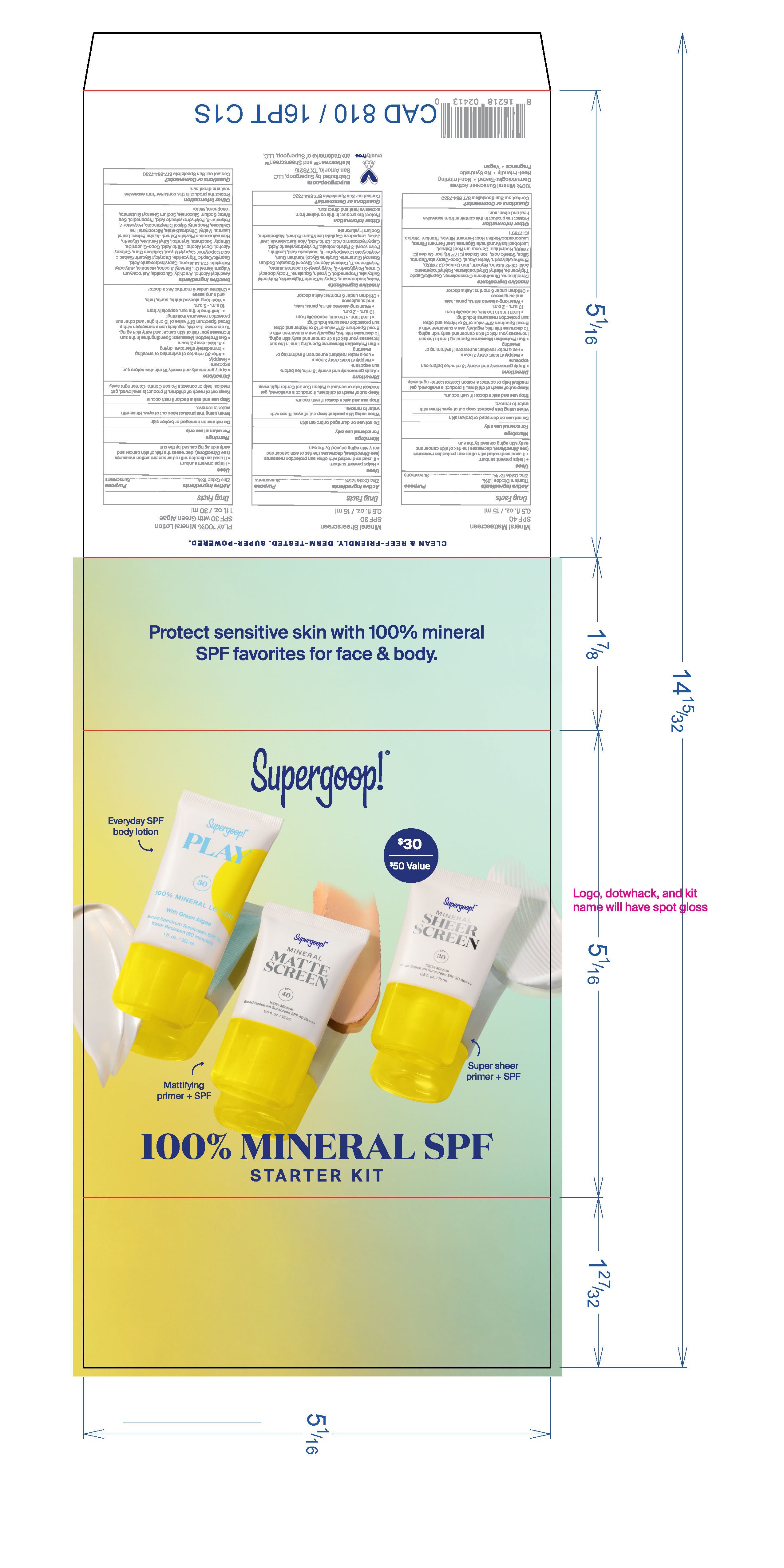 DRUG LABEL: Mineral SPF Starter Kit
NDC: 75936-610 | Form: KIT | Route: TOPICAL
Manufacturer: Supergoop, LLC
Category: otc | Type: HUMAN OTC DRUG LABEL
Date: 20230101

ACTIVE INGREDIENTS: ZINC OXIDE 17.5 g/100 mL; TITANIUM DIOXIDE 1.33 g/100 mL; ZINC OXIDE 17.42 g/100 mL; ZINC OXIDE 16 g/100 mL
INACTIVE INGREDIENTS: WATER; SQUALANE; DIMETHICONE/VINYL DIMETHICONE CROSSPOLYMER (SOFT PARTICLE); HYALURONATE SODIUM; CETOSTEARYL ALCOHOL; XANTHAN GUM; CAPRYLHYDROXAMIC ACID; ALOE VERA LEAF; GLYCERIN; MALTODEXTRIN; POLYHYDROXYSTEARIC ACID (2300 MW); POLYGLYCERYL-3 PENTARICINOLEATE; LESPEDEZA CAPITATA FLOWERING TOP; PROPANEDIOL; POLYGLYCERIN-3; POLYGLYCERYL-3 LAURATE; MEDIUM-CHAIN TRIGLYCERIDES; BUTYLOCTYL SALICYLATE; LECITHIN, SUNFLOWER; ISOSTEARIC ACID; CITRIC ACID MONOHYDRATE; ISODODECANE; SODIUM STEAROYL GLUTAMATE; BUTYLENE GLYCOL; GLYCERYL MONOSTEARATE; SODIUM CHLORIDE; AMMONIUM ACRYLOYLDIMETHYLTAURATE, DIMETHYLACRYLAMIDE, LAURYL METHACRYLATE AND LAURETH-4 METHACRYLATE COPOLYMER, TRIMETHYLOLPROPANE TRIACRYLATE CROSSLINKED (45000 MPA.S); TRIOCTYLDODECYL CITRATE; STEARIC ACID; FERRIC OXIDE YELLOW; FERRIC OXIDE RED; GLYCERIN; COCO-CAPRYLATE/CAPRATE; C9-11 ALKANE/CYCLOALKANE; WATER; ARUNDINARIA GIGANTEA WHOLE; DIMETHICONE CROSSPOLYMER (450000 MPA.S AT 12% IN CYCLOPENTASILOXANE); DIMETHICONE; POLYHYDROXYSTEARIC ACID (2300 MW); ETHYLHEXYLGLYCERIN; MEDIUM-CHAIN TRIGLYCERIDES; METHYL DIHYDROABIETATE; TOCOPHEROL; FERROSOFERRIC OXIDE; HEDYCHIUM CORONARIUM ROOT; LEUCONOSTOC/RADISH ROOT FERMENT FILTRATE; SODIUM CHLORIDE; COCO GLUCOSIDE; ERYTHRITOL; GLYCERIN; SODIUM STEAROYL GLUTAMATE; CITRIC ACID MONOHYDRATE; DOCOSANOL; ARACHIDYL ALCOHOL; ARACHIDYL GLUCOSIDE; LEVOMENOL; CAPRYLHYDROXAMIC ACID; TOCOPHEROL; DIHEPTYL SUCCINATE; POLYESTER-8 (1400 MW, CYANODIPHENYLPROPENOYL CAPPED); POLYHYDROXYSTEARIC ACID (2300 MW); PROPANEDIOL; POLYESTER-7; POTASSIUM HYDROLYZED JOJOBA ESTERS; ETHYL FERULATE; HAEMATOCOCCUS PLUVIALIS; NEOPENTYL GLYCOL DIHEPTANOATE; MICROCRYSTALLINE CELLULOSE; SODIUM GLUCONATE; CETOSTEARYL ALCOHOL; C13-15 ALKANE; WATER; CAPRYLOYL GLYCERIN/SEBACIC ACID COPOLYMER (2000 MPA.S); CAPRYLYL GLYCOL; CETYL ALCOHOL; LAURYL LAURATE; METHYL DIHYDROABIETATE; ASTROCARYUM VULGARE KERNEL OIL; BUTYLOCTYL SALICYLATE; MEDIUM-CHAIN TRIGLYCERIDES; CARBOXYMETHYLCELLULOSE SODIUM, UNSPECIFIED

Mineral SPF Starter Kit

Mineral Sheerscreen SPF 30 Active Ingredients

Zinc Oxide 17.5% Sunscreen

Mineral Mattescreen SPF 40 Active Ingredient

Titanium Dioxide 1.3% Sunscreen

Zinc Oxide 17.4% Sunscreen

Play Mineral Lotion SPF 30 Active Ingredients

Zinc Oxide 16% Sunscreen

Uses

Helps prevent sunburn

If used as directed with other sun protection measures (see Directions), decrease the risk of skin cancer and early skin aging caused by the sun

Stop use and ask a doctor if rash occurs.

WARNINGS

For External use only

Do not use on damaged or broken skin

When using this product, keep out of eyes. Rinse with water to remove.

Mineral Sheerscreen SPF 30

Apply generously and evenly as the last step in your skincare routine, before makeup and 15 minutes before sun exposure.

Reapply at least every 2 hours.

Use a water resistant sunscreen if swimming or sweating.

Sun Protection Measures: Spending time in the sun increases your risk of skin cancer and early skin aging. To decrease this risk, regularly use a sunscreen with a Broad Spectrum SPF value of 15 or higher and other sun protection measures including:

Limit time in the sun, especially from 10 a.m.- 2 p.m.

Wear long-sleeved shirts, pants, hats, and sunglasses

Children under 6 months: Ask a doctor

Mineral Mattescreen SPF 40

Directions

Apply generously and evenly as the last step in your skincare routine, before makeup and 15 minutes before sun exposure.

Reapply at least every 2 hours.

Use a water resistant sunscreen if swimming or sweating.

Sun Protection Measures: Spending time in the sun increases your risk of skin cancer and early skin aging. To decrease this risk, regularly use a sunscreen with a Broad Spectrum SPF value of 15 or higher and other sun protection measures including:

Limit time in the sun, especially from 10 a.m.- 2 p.m.

Wear long-sleeved shirts, pants, hats, and sunglasses

Children under 6 months: Ask a doctor

Play 100% Mineral Lotion SPF 30

Directions

• apply generously and evenly 15 minutes before sun exposure
• reapply:
• after 80 minutes of swimming or sweating
• immediately after towel drying
• at least every 2 hours

Sun Protection Measures: Spending time in the sun increases your risk of skin cancer and early skin aging. To decrease this risk, regularly use a sunscreen with a Broad Spectrum SPF value of 15 or higher and other sun protection measures including:

Limit time in the sun, especially from 10 a.m.- 2 p.m.

Wear long-sleeved shirts, pants, hats, and sunglasses

Children under 6 months: Ask a doctor

Keep out of reach of children. If product is swallowed, get medical help, or contact a poison control center right away.

Mineral Sheerscreen SPF 30

Inactive Ingredients: Water, Isododecane, Caprylic/Capric Triglyceride, Butyloctyl Salicylate, Propanediol, Glycerin, Squalane, Trioctyldodecyl Citrate, Polyglycerin-3, Polyglyceryl-3 Lactate/Laurate, Polysilicone-11, Cetearyl Alcohol, Glyceryl Stearate, Sodium Stearoyl Glutamate, Butylene Glycol, Xanthan Gum, Polyacrylate Crosspolymer-6, Isostearic Acid, Lecithin, Polyglyceryl-3 Polyricinoleate, Polyhydroxystearic Acid, Caprylhydroxamic Acid, Citric Acid, Aloe Barbadensis Leaf Juice, Lespedeza Capitata Leaf/Stem Extract, Maltodextrin, Sodium Hyaluronate

Mineral Mattescreen SPF 40

Inactive Ingredients: Dimethicone, Dimethicone Crosspolymer, Caprylic/Capric Triglyceride, Methyl Dihydroabietate, Polyhydroxystearic Acid, C9-12 Alkane, Glycerin, Iron Oxides (CI 77492), Ethylhexylglycerin, Water (Aqua), Coco-Caprylate/Caprate, Silica, Stearic Acid, Iron Oxides (CI 77491), Iron Oxides (CI 77499), Hedychium Coronarium Root Extract, Lactobacillus/Arundinaria Gigantea Leaf Ferment Filtrate, Leuconostoc/Radish Root Ferment Filtrate, Titanium Dioxide (CI 77891)

Play 100% Mineral Lotion SPF 30

Inactive Ingredients: Arachidyl Alcohol, Arachidyl Glucoside, Astrocaryum Vulgare Kernel Oil, Behenyl Alcohol, Bisabolol, Butyloctyl Salicylate, C13-14 Alkane, Caprylhydroxamic Acid, Caprylic/Capric Triglyceride, Capryloyl Glycerin/Sebacic Acid Copolymer, Caprylyl Glycol, Cellulose Gum, Cetearyl Alcohol, Cetyl Alcohol, Citric Acid, Coco-Glucoside, Diheptyl Succinate, Erythritol, Ethyl Ferulate, Glycerin, Haematococcus Pluvialis Extract, Jojoba Esters, Lauryl Laurate, Methyl Dihydroabietate, Microcrystalline Cellulose, Neopentyl Glycol Diheptanoate, Polyester-7, Polyester-8, Polyhydroxystearic Acid, Propanediol, Sea Water, Sodium Gluconate, Sodium Stearoyl Glutamate, Tocopherol, Water

PACKAGE LABEL

Supergoop!
100% Mineral SPF
Starter Kit
Protect sensitive skin with 100% mineral SPF favorites for face & body